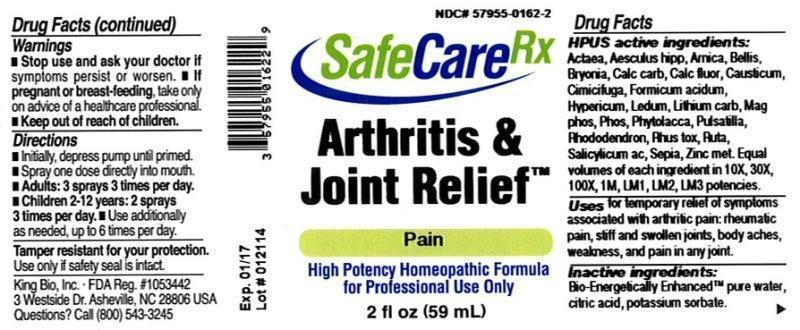 DRUG LABEL: Arthritis and Joint Relief
NDC: 57955-0162 | Form: LIQUID
Manufacturer: King Bio Inc.
Category: homeopathic | Type: HUMAN OTC DRUG LABEL
Date: 20140417

ACTIVE INGREDIENTS: ACTAEA SPICATA ROOT 10 [hp_X]/59 mL; HORSE CHESTNUT 10 [hp_X]/59 mL; ARNICA MONTANA 10 [hp_X]/59 mL; BELLIS PERENNIS 10 [hp_X]/59 mL; BRYONIA ALBA ROOT 10 [hp_X]/59 mL; OYSTER SHELL CALCIUM CARBONATE, CRUDE 10 [hp_X]/59 mL; CALCIUM FLUORIDE 10 [hp_X]/59 mL; CAUSTICUM 10 [hp_X]/59 mL; BLACK COHOSH 10 [hp_X]/59 mL; FORMIC ACID 10 [hp_X]/59 mL; HYPERICUM PERFORATUM 10 [hp_X]/59 mL; LEDUM PALUSTRE TWIG 10 [hp_X]/59 mL; LITHIUM CARBONATE 10 [hp_X]/59 mL; MAGNESIUM PHOSPHATE, DIBASIC TRIHYDRATE 10 [hp_X]/59 mL; PHYTOLACCA AMERICANA ROOT 10 [hp_X]/59 mL; PULSATILLA VULGARIS 10 [hp_X]/59 mL; RHODODENDRON AUREUM LEAF 10 [hp_X]/59 mL; TOXICODENDRON PUBESCENS LEAF 10 [hp_X]/59 mL; RUTA GRAVEOLENS FLOWERING TOP 10 [hp_X]/59 mL; SALICYLIC ACID 10 [hp_X]/59 mL; SEPIA OFFICINALIS JUICE 10 [hp_X]/59 mL; ZINC 10 [hp_X]/59 mL
INACTIVE INGREDIENTS: WATER; POTASSIUM SORBATE; CITRIC ACID MONOHYDRATE

Arthritis and Joint Relief™

ACTIVE INGREDIENT

Drug Facts__________________________________________________________________________________________________________

HPUS active ingredients: Actaea spicata, Aesculus hippocastanum, Arnica montana, Bellis perennis, Bryonia, Calcarea carbonica, Calcarea fluorica, Causticum, Cimicifuga racemosa, Formicum acidum, Hypericum perforatum, Ledum palustre, Lithium carbonicum, Magnesia phosphorica, Phytolacca decandra, Pulsatilla, Rhododendron chrysanthum, Rhus toxicodendron, Ruta graveolens, Salicylicum acidum, Sepia, Zincum metallicum. Equal volumes of each ingredient in 10X, 30X, 100X, 1M, LM1, LM2, LM3 potencies.

INDICATIONS AND USAGE

Uses for temporary relief of symptoms associated with arthritic pain: rheumatic pain, stiff and swollen joints, body aches, weakness, and pain in any joint.

Inactive Ingredients:

Bio-Energetically Enhanced™ pure water, citric acid and potassium sorbate.

Warnings

- Stop use and ask your doctor if symptoms persist or worsen.
- If pregnant or breast-feeding, take only on advice of a healthcare professional.

- Keep out of reach of children.

Directions

- Initially, depress pump until primed.
- Spray one dose directly into mouth.
- Adults: 3 sprays 3 times per day.
- Children 2-12 years: 2 sprays 3 times per day.
- Use additionally as needed, up to 6 times per day.

OTHER SAFETY INFORMATION

Tamper resistant for your protection. Use only if safety seal is intact.

PURPOSE

Uses for temporary relief of symptoms associated with arthritic pain:

- rheumatic pain
- stiff and swollen joints
- body aches
- weakness
- pain in any joint